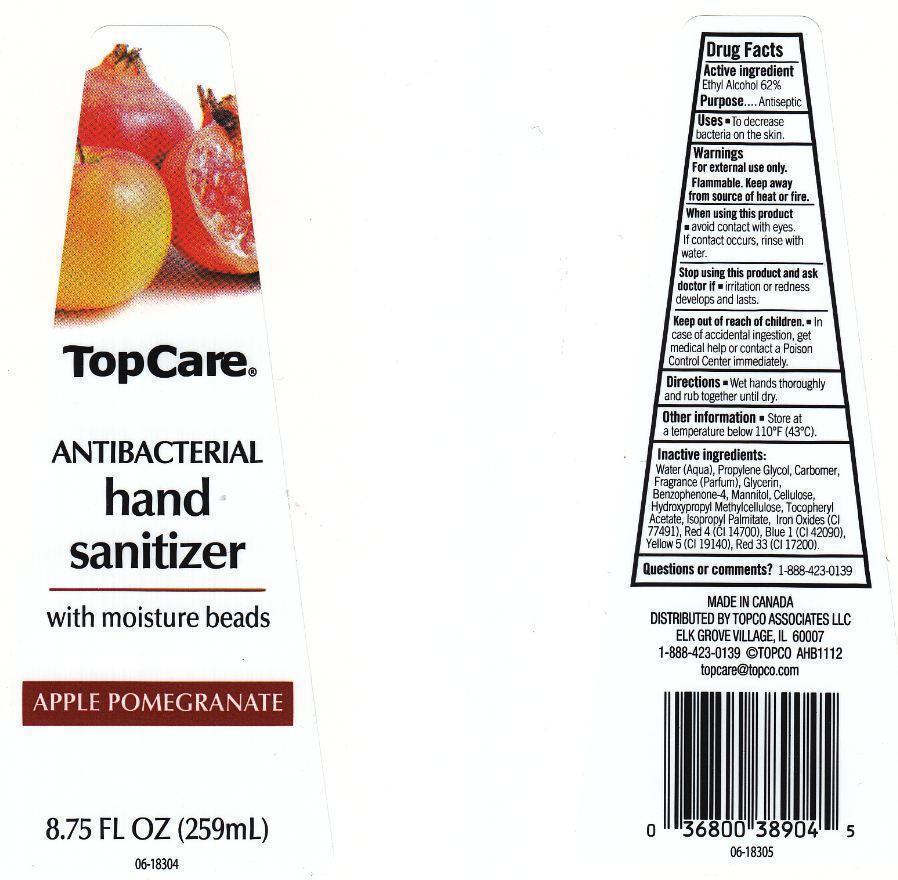 DRUG LABEL: TOPCARE
NDC: 36800-262 | Form: LIQUID
Manufacturer: TOPCO ASSOCIATES LLC
Category: otc | Type: HUMAN OTC DRUG LABEL
Date: 20130319

ACTIVE INGREDIENTS: ALCOHOL 620 mg/1 mL
INACTIVE INGREDIENTS: WATER; PROPYLENE GLYCOL; CARBOMER 934; GLYCERIN; SULISOBENZONE; MANNITOL; POWDERED CELLULOSE; HYPROMELLOSES; .ALPHA.-TOCOPHEROL ACETATE; ISOPROPYL PALMITATE; FERRIC OXIDE RED; FD&C RED NO. 4; FD&C BLUE NO. 1; FD&C YELLOW NO. 5; D&C RED NO. 33

DRUG FACTS

ACTIVE INGREDIENT

ETHYL ALCOHOL 62%

PURPOSE

ANTISEPTIC

USES

TO DECREASE BACTERIA ON THE SKIN.

WARNINGS

FOR EXTERNAL USE ONLY. FLAMMABLE. KEEP AWAY FROM SOURCE OF HEAT OR FIRE.

WHEN USING THIS PRODUCT

AVOID CONTACT WITH EYES. IF CONTACT OCCURS, RINSE WITH WATER.

STOP USING THIS PRODUCT AND ASK DOCTOR IF

IRRITATION OR REDNESS DEVELOPS AND LASTS.

KEEP OUT OF REACH OF CHILDREN

IN CASE OF ACCIDENTAL INGESTION, GET MEDICAL HELP OR CONTACT A POISON CONTROL CENTER IMMEDIATELY.

DIRECTIONS

WET HANDS THOROUGHLY AND RUB TOGETHER UNTIL DRY.

OTHER INFORMATION

STORE AT A TEMPERATURE BELOW 110F (43C).

INACTIVE INGREDIENTS

WATER (AQUA), PROPYLENE GLYCOL, CARBOMER, FRAGRANCE (PARFUM), GLYCERIN, BENZOPHENONE-4, MANNITOL, CELLULOSE, HYDROXYPROPYL METHYLCELLULOSE, TOCOPHERYL ACETATE, ISOPROPYL PALMITATE, IRON OXIDES (CI 77491), RED 4 (CI 14700), BLUE 1 (CI 42090), YELLOW 5 (CI 19140), RED 33 (CI 17200).

QUESTIONS OR COMMENTS?

1-888-423-0139